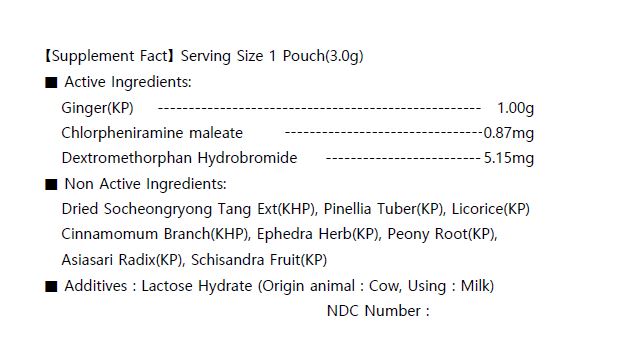 DRUG LABEL: SoCheongRyong Tang Extract
NDC: 73442-0012 | Form: GRANULE
Manufacturer: I World Pharmaceutical Co., Ltd.
Category: otc | Type: HUMAN OTC DRUG LABEL
Date: 20200916

ACTIVE INGREDIENTS: GINGER 1 g/3 g; DEXTROMETHORPHAN HYDROBROMIDE 0.00515 g/3 g; CHLORPHENIRAMINE MALEATE 0.00087 g/3 g
INACTIVE INGREDIENTS: LACTOSE MONOHYDRATE

ACTIVE INGREDIENT

Ginger(KP)
Chlorpheniramine maleate
Dextromethorphan Hydrobromide

PURPOSE

bronchitis, bronchial asthma, runny nose, phlegm cough, rhinitis

Keep out of reach of children

INDICATIONS AND USAGE

for adults take 1 pouch per intake, 3 times a day, before or between meals

Keep out of reach of children. In case of overdose, get medical help or contact a Poison Control Center right away.

INACTIVE INGREDIENT

Dried Socheongryong Tang Ext(KHP), Pinellia Tuber(KP), Licorice(KP), Cinnamomum Branch(KHP), Ephedra Herb(KP), Peony Root(KP), Asiasari Radix(KP), Schisandra Fruit(KP)

DOSAGE AND ADMINISTRATION

For oral use only